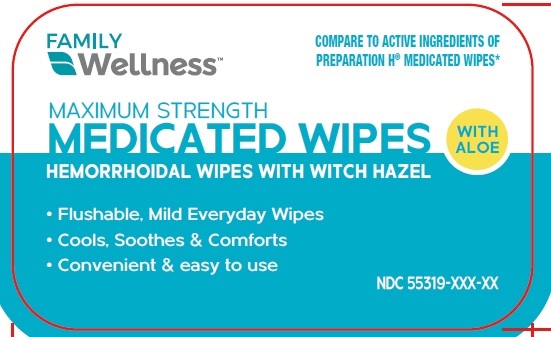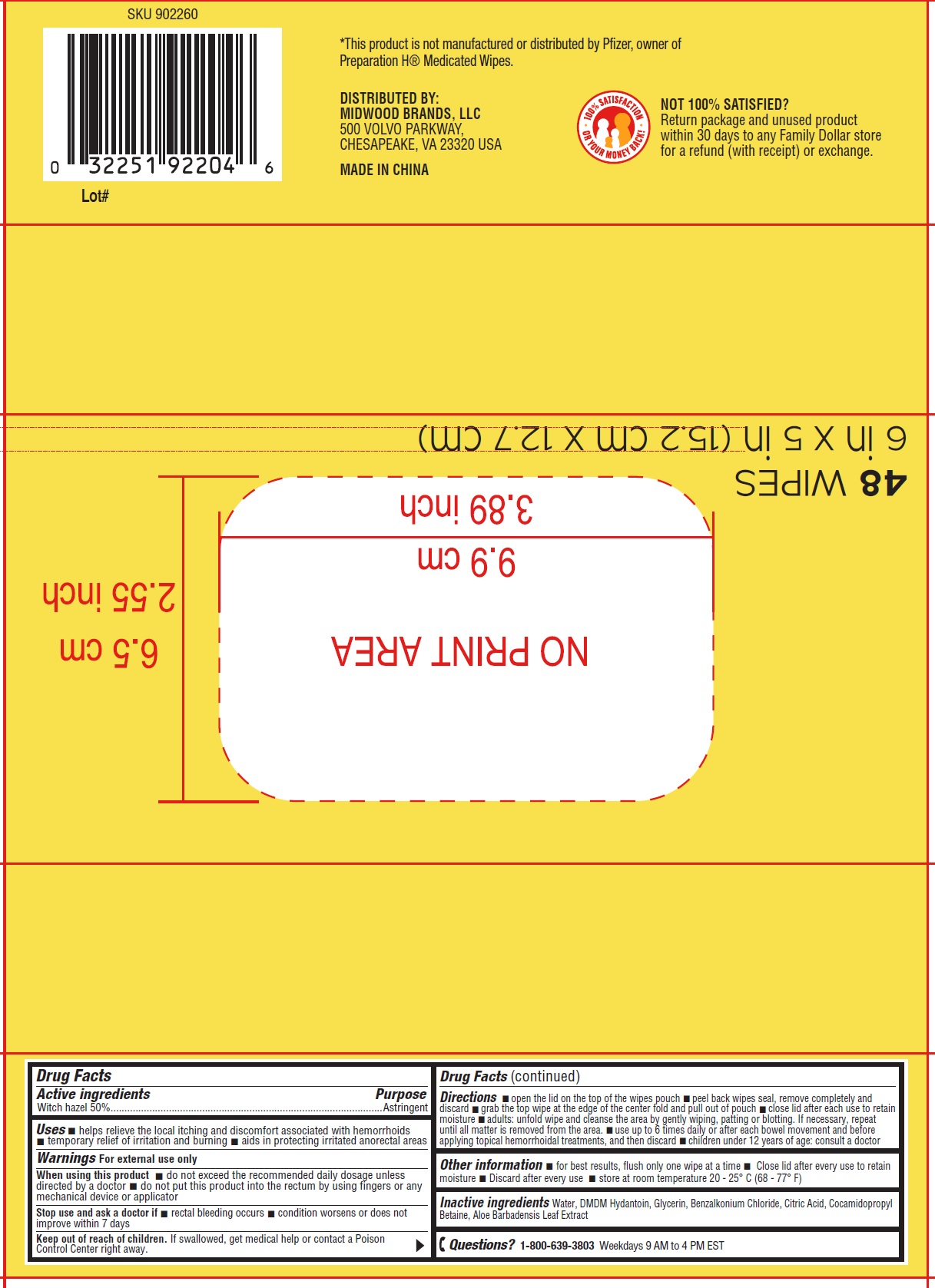 DRUG LABEL: Medicated Wipes Hemorroidal Wipes With Witch Hazel
NDC: 72932-009 | Form: CLOTH
Manufacturer: Wuhan Zonsen Medical Products Co., Ltd.
Category: otc | Type: HUMAN OTC DRUG LABEL
Date: 20240226

ACTIVE INGREDIENTS: WITCH HAZEL 500 mg/1 mL
INACTIVE INGREDIENTS: WATER; DMDM HYDANTOIN; GLYCERIN; BENZALKONIUM CHLORIDE; CITRIC ACID MONOHYDRATE; COCAMIDOPROPYL BETAINE; ALOE VERA LEAF

Medicated Wipes Hemorroidal Wipes With Witch Hazel

Active ingredients

Witch hazel 50%

Purpose

Astringent

Uses

- helps relieve the local itching and discomfort associated with hemorrhoids
- temporary relief of irritation and burning
- aids in protecting irritated anorectal areas

Warnings

For external use only

When using this product

- do not exceed the recommended daily dosage unless directed by a doctor
- do not put this product into the rectum by using fingers or any mechanical device or applicator

Stop use and ask a doctor if

- rectal bleeding occurs
- condition worsens or does not improve within 7 days

Keep out of reach of children.

If swallowed, get medical help or contact a Poison Control Center right away.

Directions

- open the lid on the top of the wipes pouch
- peel back wipes seal, remove completely and discard
- grab the top wipe at the edge of the center fold and pull out of pouch
- close lid after each use to retain moisture
- adults: unfold wipe and cleanse the area by gently wiping, patting or blotting. If necessary, repeat until all matter is removed from the area.
- se up to 6 times daily or after each bowel movement and before applying topical hemorrhoidal treatments, and then discard
- children under 12 years of age: consult a doctor

Other information

- for best results, flush only one wipe at a time
- Close lid after every use to retain moisture
- Discard after every use
- store at room temperature 20 - 25° C (68 - 77° F)

Inactive ingredients

Water, DMDM Hydantoin, Glycerin, Benzalkonium Chloride, Citric Acid, Cocamidopropyl Betaine, Aloe Barbadensis Leaf Extract

Questions?

1-800-639-3803Weekdays 9 AM to 4 PM EST